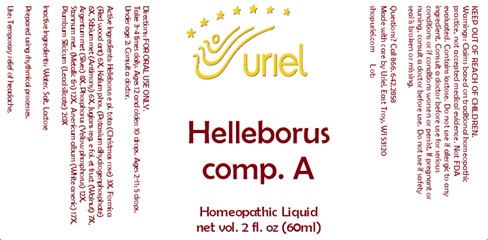 DRUG LABEL: Helleborus comp. A
NDC: 48951-5136 | Form: LIQUID
Manufacturer: Uriel Pharmacy, Inc.
Category: homeopathic | Type: HUMAN OTC DRUG LABEL
Date: 20241217

ACTIVE INGREDIENTS: FORMICA RUFA 6 [hp_X]/1 mL; ANTIMONY 6 [hp_X]/1 mL; SILVER 8 [hp_X]/1 mL; HELLEBORUS FOETIDUS ROOT 3 [hp_X]/1 mL; POTASSIUM PHOSPHATE, MONOBASIC 6 [hp_X]/1 mL; ARSENIC TRIOXIDE 17 [hp_X]/1 mL; TIN 12 [hp_X]/1 mL; PHOSPHORUS 12 [hp_X]/1 mL; JUGLANS REGIA LEAF 7 [hp_X]/1 mL; LEAD MONOSILICATE 20 [hp_X]/1 mL
INACTIVE INGREDIENTS: WATER; LACTOSE, UNSPECIFIED FORM; SODIUM CHLORIDE

Helleborus comp. A

INDICATIONS AND USAGE

Directions: FOR ORAL USE ONLY.

DOSAGE AND ADMINISTRATION

Take 3-4 times daily. Ages 12 and older: 10 drops. Ages 2-11: 5 drops. Under age 2: Consult a doctor.

ACTIVE INGREDIENT

Active Ingredients: Helleborus e pl. tota (christmas rose) 3X, Formica (red wood ant) 6X, Kalium phos. (potassium dihydrogenphosphate) 6X, Stibium met (antimony) 6X, Juglans reg. e fol. et fruct (walnut) 7X, Argentum met (silver) 8X, Phosphorus (yellow phosphorus) 12X, Stannum met. (metallic tin) 12X, Arsenicum album (white arsenic) 17X, Plumbum Silicicum (lead silicate) 20X

Inactive Ingredients: Water, Salt, Lactose

Prepared using rhythmical processes.

PURPOSE

Use: Temporary relief of headache.

KEEP OUT OF REACH OF CHILDREN.

WARNINGS

Warnings: Claims based on traditional homeopathic practice, not accepted medical evidence. Not FDA evaluated. Contains traces of lactose. Do not use if allergic to any ingredient. Consult a doctor before use for serious conditions or if conditions worsen or persist. If pregnant or nursing, consult a doctor before use. Do not use if safety seal is broken or missing.